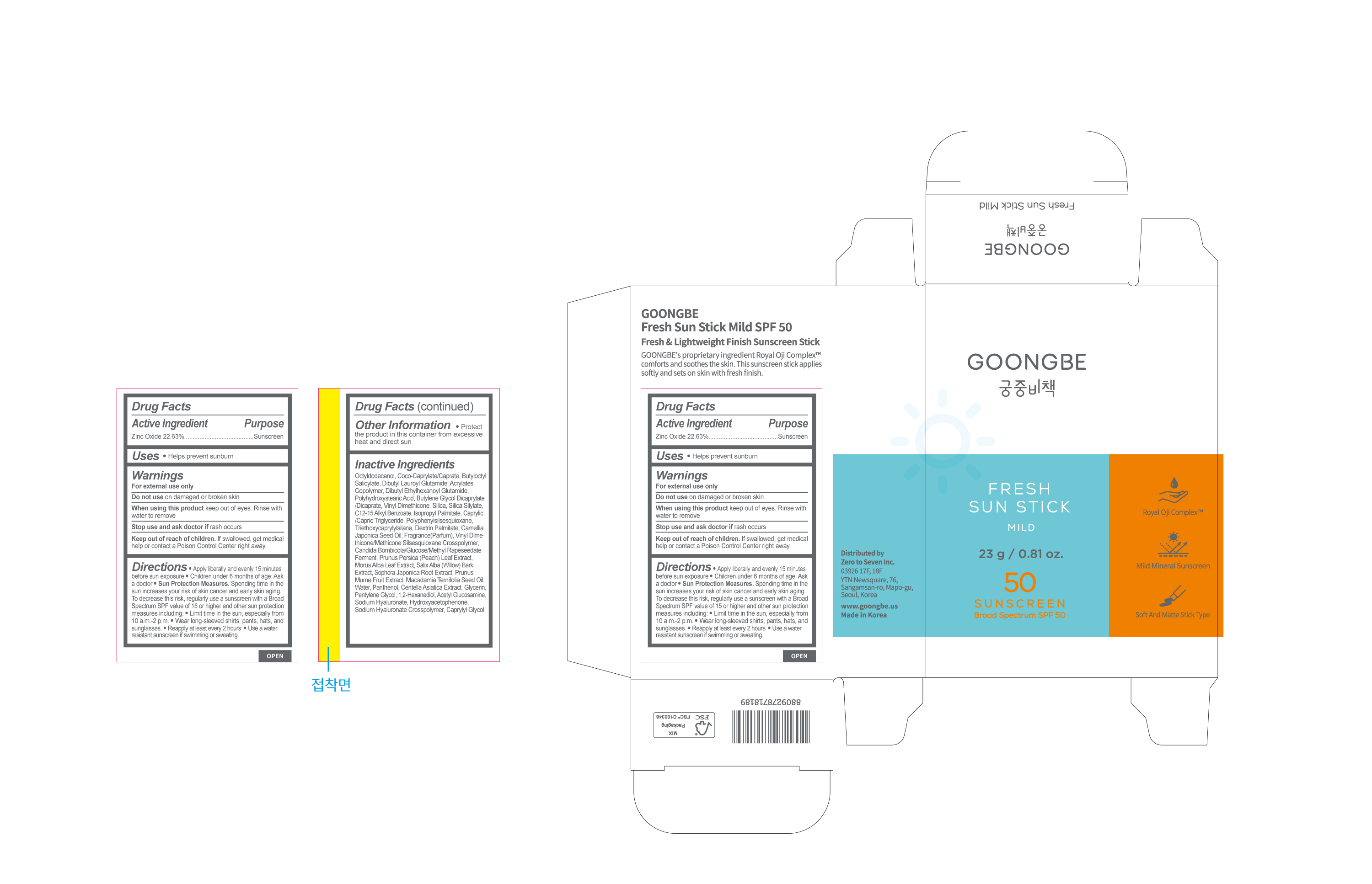 DRUG LABEL: GOONGBE Fresh Sun Stick Mild SPF 50
NDC: 43319-073 | Form: STICK
Manufacturer: Zero to Seven Inc.
Category: otc | Type: HUMAN OTC DRUG LABEL
Date: 20241118

ACTIVE INGREDIENTS: ZINC OXIDE 22.63 g/100 g
INACTIVE INGREDIENTS: DIBUTYL LAUROYL GLUTAMIDE; BUTYLOCTYL SALICYLATE; OCTYLDODECANOL; COCO-CAPRYLATE/CAPRATE

Dosage & Administration

Dosage form: Stick

Administration: Topical

Warnings

For external use only

Do not use on damaged or broken skin.

When using this product keep out of eyes.

Rinse with water to remove Stop use and ask doctor if rash occurs

Keep out of reach of children. If swallowed, get medical help or contact a Poison Control Center right away

Inactive Ingredients

Octyldodecanol, Coco-Caprylate/Caprate, Butyloctyl Salicylate, Dibutyl Lauroyl Glutamide, Acrylates Copolymer, Dibutyl Ethylhexanoyl Glutamide, Polyhydroxystearic Acid, Butylene Glycol Dicaprylate /Dicaprate, Vinyl Dimethicone, Silica, Silica Silylate, C12-15 Alkyl Benzoate, Isopropyl Palmitate, Caprylic /Capric Triglyceride, Polyphenylsilsesquioxane, Triethoxycaprylylsilane, Dextrin Palmitate, Camellia Japonica Seed Oil, Fragrance(Parfum), Vinyl Dime thicone/Methicone Silsesquioxane Crosspolymer, Candida Bombicola/Glucose/Methyl Rapeseedate Ferment, Prunus Persica (Peach) Leaf Extract, Morus Alba Leaf Extract, Salix Alba (Willow) Bark Extract, Sophora Japonica Root Extract, Prunus Mume Fruit Extract, Macadamia Ternifolia Seed Oil, Water, Panthenol, Centella Asiatica Extract, Glycerin, Pentylene Glycol, 1,2-Hexanediol, Acetyl Glucosamine, Sodium Hyaluronate, Hydroxyacetophenone, Sodium Hyaluronate Crosspolymer, Caprylyl Glycol

Usage

Helps prevent sunburn

Keep out of reach of children.

If swallowed, get medical help or contact a Poison Control Center right away.

Purpose

sunscreen